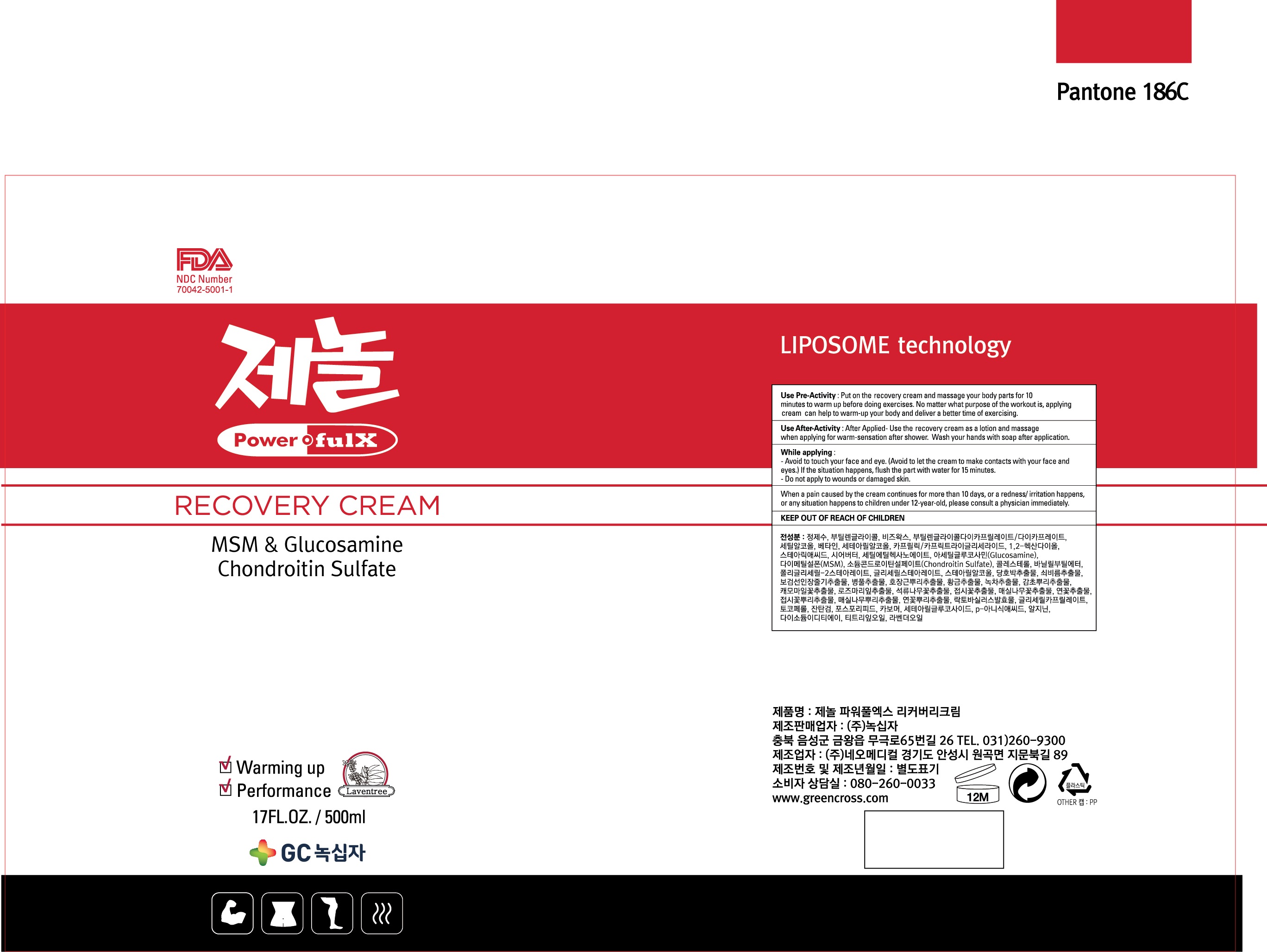 DRUG LABEL: ZENOL POWERFULX RECOVERYCREAM
NDC: 70042-0001 | Form: CREAM
Manufacturer: Powerful X
Category: otc | Type: HUMAN OTC DRUG LABEL
Date: 20180829

ACTIVE INGREDIENTS: STEARIC ACID 1.5 g/100 mL
INACTIVE INGREDIENTS: WATER; BUTYLENE GLYCOL

Drug Facts

ACTIVE INGREDIENT

Stearic Acid

INACTIVE INGREDIENT

Water, Butylene Glycol, etc

PURPOSE

Warm up pre/after-execise and after shower

keep out of reach of the children

WARNINGS

1. Do not use in the following cases(Eczema and scalp wounds)
2.Side Effects
1)Due to the use of this druf if rash, irritation, itching and symptopms of hypersnesitivity occur dicontinue use and consult your phamacisr or doctor
3.General Precautions
1)If in contact with the eyes, wash out thoroughty with water If the symptoms are servere, seek medical advice immediately
2)This product is for exeternal use only. Do not use for internal use
4.Storage and handling precautions
1)If possible, avoid direct sunlight and store in cool and area of low humidity
2)In order to maintain the quality of the product and avoid misuse
3)Avoid placing the product near fire and store out in reach of children

DOSAGE AND ADMINISTRATION

for external use only

INDICATIONS AND USAGE

Put on the cream and massage your body parts for 10 minutes to warm up before doing exercise.

Apply cream and massge when applying for warm-sensation after shower.